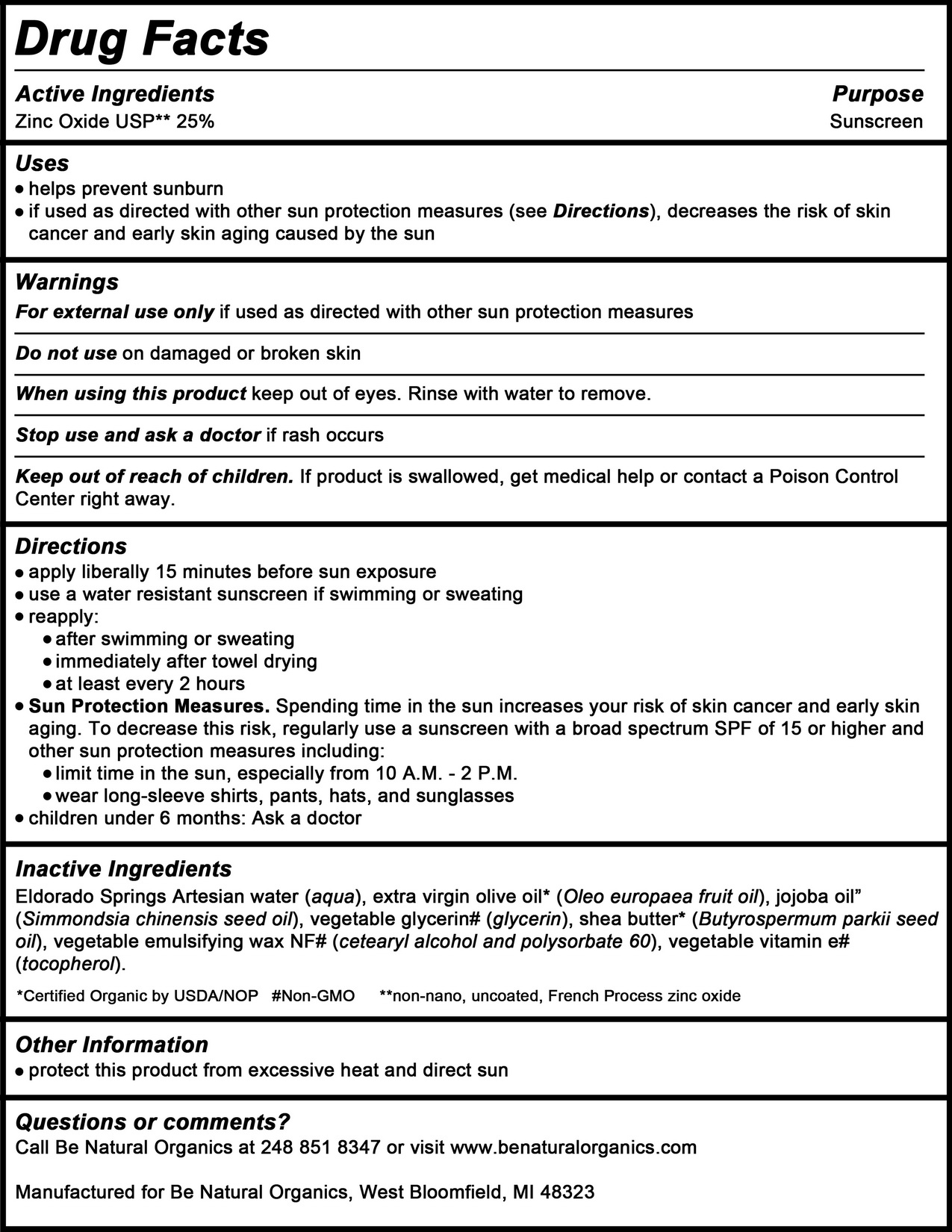 DRUG LABEL: Be Natural Organics Broad Spectrum Tint Free SPF 30
NDC: 73369-1001 | Form: CREAM
Manufacturer: Kabana Skin Care
Category: otc | Type: HUMAN OTC DRUG LABEL
Date: 20241023

ACTIVE INGREDIENTS: ZINC OXIDE 25 g/100 g
INACTIVE INGREDIENTS: CETOSTEARYL ALCOHOL 1.125 g/100 g; POLYSORBATE 60 1.125 g/100 g; WATER 35 g/100 g; OLIVE OIL 26.95 g/100 g; SHEA BUTTER 1.93 g/100 g; GLYCERIN 3.75 g/100 g; JOJOBA OIL 3.75 g/100 g; ALPHA-TOCOPHEROL 1.38 g/100 g

Drug Facts

Active Ingredients

Zinc Oxide USP** 25%

Purpose

Sunscreen

Uses

- Helps prevent sunburn
- if used as directed with other sun protection measures (see Directions), decreases the risk of skin cancer and early skin aging caused by the sun

Do not use on damaged or broken skin

When using this product keep out of eyes. Rinse with water to remove.

Stop use and ask a doctor if rash occurs

Keep out of reach of children, if product is swallowed, get medical help or contact a Poison Control Center right away.

Inactive Ingredients

Eldorado Springs Artesian water (aqua), extra virgin olive oil* (Oleo europaea fruit oil), jojoba oil* (Simmondsia chinensis seed oil), vegetable glycerin# (glycerin), shea butter* (Butyrospermum parkii seed oil), vegetable emulsifying wax NF# (cetearyl alcohol and polysorbate 60), vegetable vitamin e# (tocopherol).

*Certified Organic by USDA/NOP #Non-GMO **non-nano, uncoated, French Process zinc oxide

Warnings

For external use only if used as directed with other sun protection measures

Directions

- apply liberally 15 minutes before sun exposure
- use a water resistant sunscreen if swimming or sweating
- reapply:
  - after swimming or sweating
  - immediately after towel drying
  - at least every 2 hours.
- Sun Protection Measures. Spending time in the sun increases your risk of skin cancer and early skin aging. To decrease this risk, regularly use a sunscreen with a Broad Spectrum SPF value of 15 or higher and other sun protection measures including:
- Limit time in the sun, especially from 10 AM – 2 PM.
- Wear long-sleeved shirts, pants, hats and sunglasses.
- Children under 6 months. Ask a doctor

RECENT MAJOR CHANGES

- Apply liberally 15 minutes before sun exposure
- Use a water resistant sunscreen if swimming or sweating
- Reapply at least every 2 hours

DOSAGE AND ADMINISTRATION

- Apply liberally 15 minutes before sun exposure
- Use a water resistant sunscreen if swimming or sweating
- Reapply at least every 2 hours

Questions or comments?

Call Be Natural Organics at 248 851 8347 or visit www.benaturalorganics.com

Manufactured for Be Natural Organics, West Bloomfield, MI 48323

Other Information

- protect this product from excessive heat and direct sun